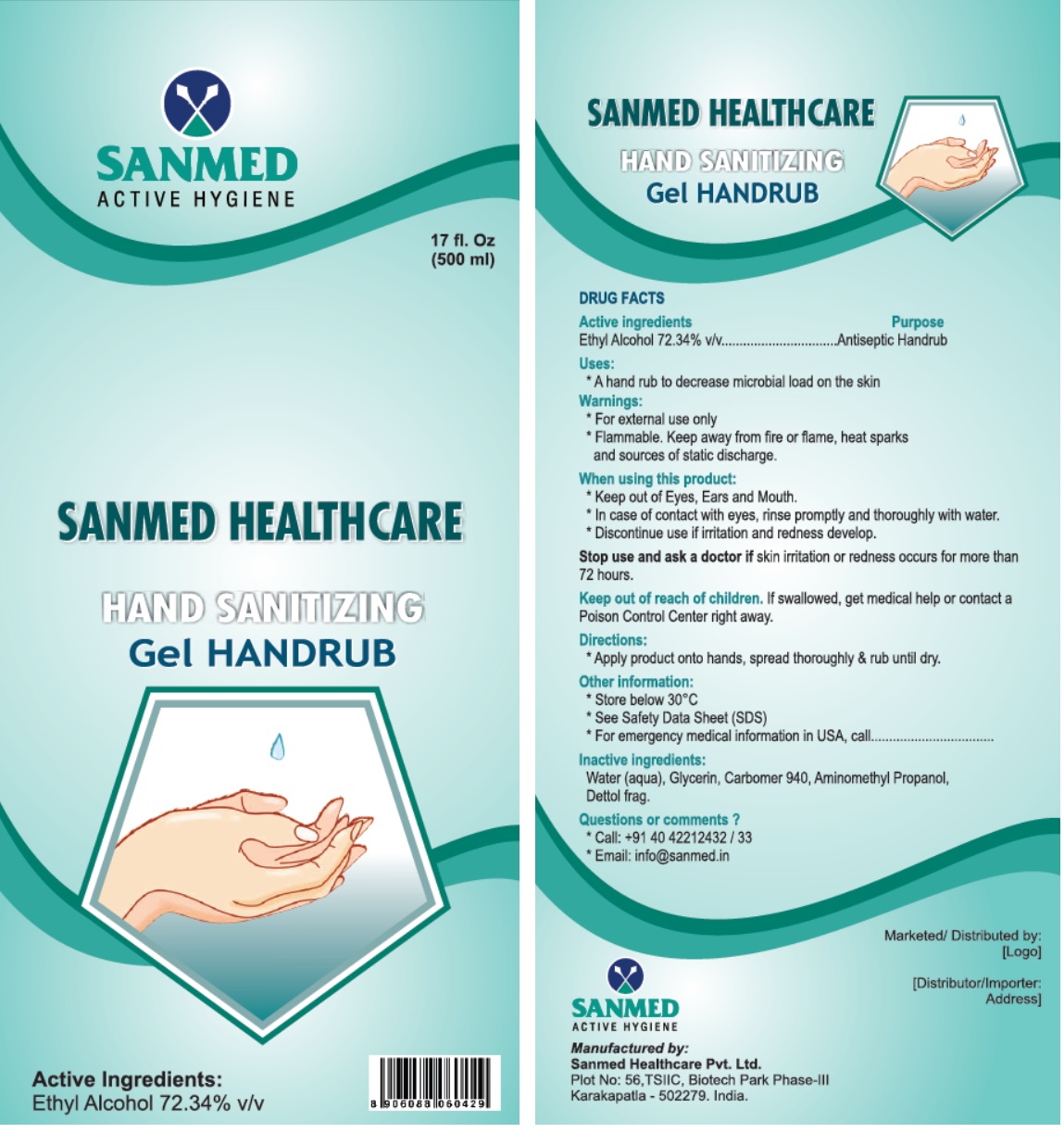 DRUG LABEL: SANMED HEALTHCARE HAND SANITIZING Gel HANDRUB
NDC: 81357-100 | Form: GEL
Manufacturer: Sanmed Healthcare Private Limited
Category: otc | Type: HUMAN OTC DRUG LABEL
Date: 20210521

ACTIVE INGREDIENTS: ALCOHOL 72.34 mL/100 mL
INACTIVE INGREDIENTS: WATER; GLYCERIN; CARBOMER HOMOPOLYMER TYPE C (ALLYL PENTAERYTHRITOL CROSSLINKED); AMINOMETHYLPROPANOL

SANMED HEALTHCARE HAND SANITIZING Gel HANDRUB

Active ingredients

Ethyl Alcohol 72.34% v/v

Purpose

Antiseptic Handrub

Uses:

* A hand rub to decrease microbial load on the skin

Warnings:

* For external use only
* Flammable. Keep away from fire or flame, heat sparks and sources of static discharge.

When using this product:
* Keep out of Eyes, Ears and Mouth.
* In case of contact with eyes, rinse promptly and thoroughly with water.
* Discontinue use if irritation and redness develop.

Stop use and ask a doctor if skin irritation or redness occurs for more than 72 hours.

Keep out of reach of children. If swallowed, get medical help or contact a Poison Control Center right away.

Directions:

* Apply product onto hands, spread thoroughly & rub until dry.

Other information:

* Store below 30°C
* See Safety Data Sheet (SDS)
* For emergency medical information in USA, call

Inactive ingredients:

Water (aqua), Glycerin, Carbomer 940, Aminomethyl Propanol, Dettol frag.

Questions or comments?

* Call: +91 40 42212432 / 33
* Email: info@sanmed.in

SANMED ACTIVE HYGIENE

Manufactured by:
Sanmed Healthcare Pvt. Ltd.
Plot No: 56, TSIIC, Biotech Park Phase-III
Karakapatla - 502279. India.